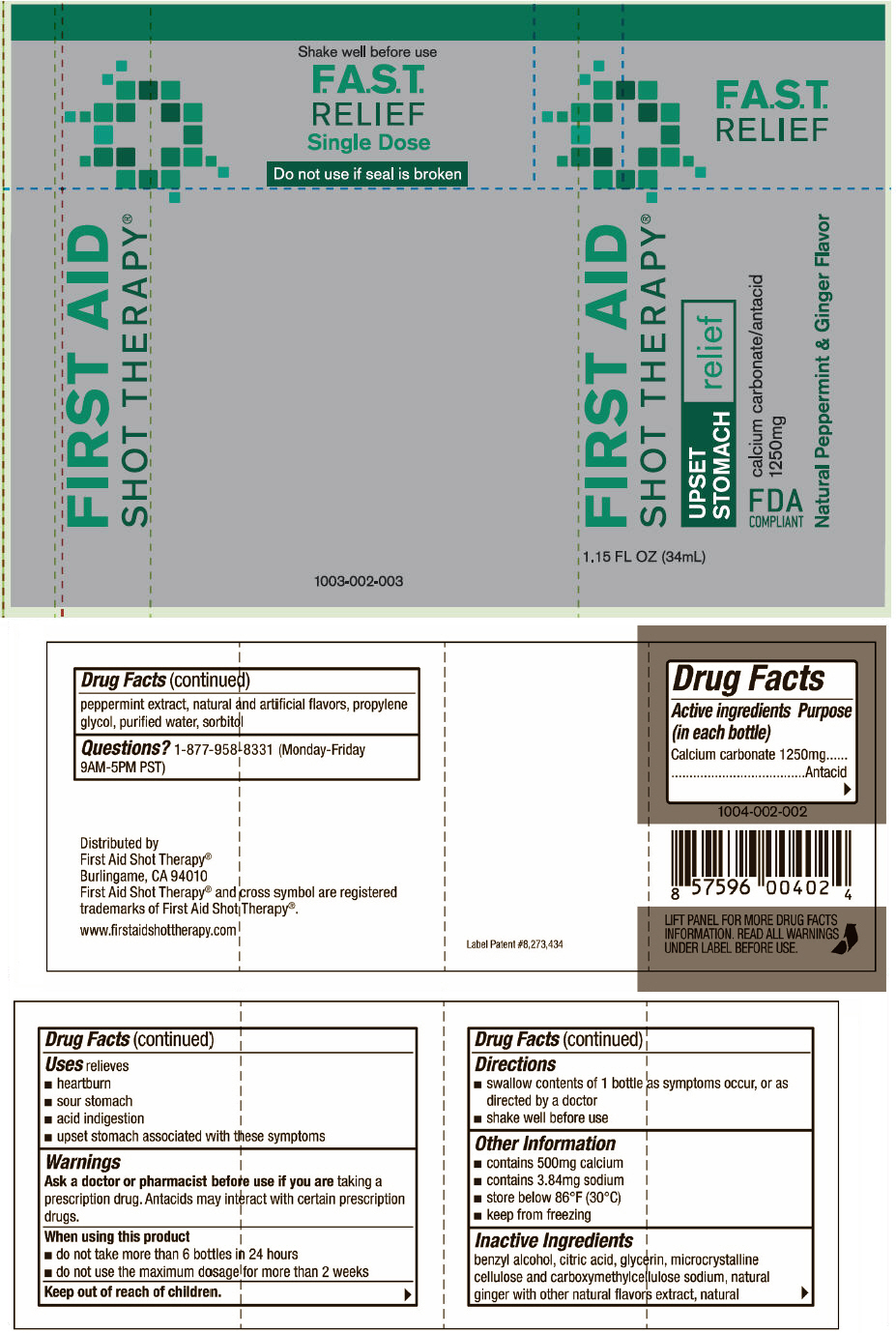 DRUG LABEL: First Aid Shot Therapy Upset Stomach Relief
NDC: 57815-021 | Form: SOLUTION
Manufacturer: First Aid Beverages, Inc.
Category: otc | Type: HUMAN OTC DRUG LABEL
Date: 20140117

ACTIVE INGREDIENTS: Calcium Carbonate 1250 mg/34 mL
INACTIVE INGREDIENTS: Benzyl Alcohol; Anhydrous Citric Acid; Glycerin; Cellulose, Microcrystalline; Propylene Glycol; Water; Sorbitol

First Aid Shot Therapy® Upset Stomach Relief

Drug Facts

Active ingredients (in each bottle)

Calcium carbonate 1250mg

Purpose

Antacid

Uses

relieves

- heartburn
- sour stomach
- acid indigestion
- upset stomach associated with these symptoms

Warnings

Ask a doctor or pharmacist before use if you are taking a prescription drug. Antacids may interact with certain prescription drugs.

When using this product

- do not take more than 6 bottles in 24 hours
- do not use the maximum dosage for more than 2 weeks

Keep out of reach of children.

Directions

- swallow contents of 1 bottle as symptoms occur, or as directed by a doctor
- shake well before use

Other Information

- contains 500mg calcium
- contains 3.84mg sodium
- store below 86°F (30°C)
- keep from freezing

Inactive Ingredients

benzyl alcohol, citric acid, glycerin, microcrystalline cellulose and carboxymethylcellulose sodium, natural ginger with other natural flavors extract, natural peppermint extract, natural and artificial flavors, propylene glycol, purified water, sorbitol

Questions?

1-877-958-8331 (Monday-Friday 9AM-5PM PST)

Distributed by
First Aid Shot Therapy®
Burlingame, CA 94010

PRINCIPAL DISPLAY PANEL - 34 mL Bottle Label

F.A.S.T.
RELIEF

FIRST AID
SHOT THERAPY®

UPSET
STOMACH
relief

calcium carbonate/antacid
1250mg

FDA
COMPLIANT

Natural Peppermint & Ginger Flavor

1.15 FL OZ (34mL)